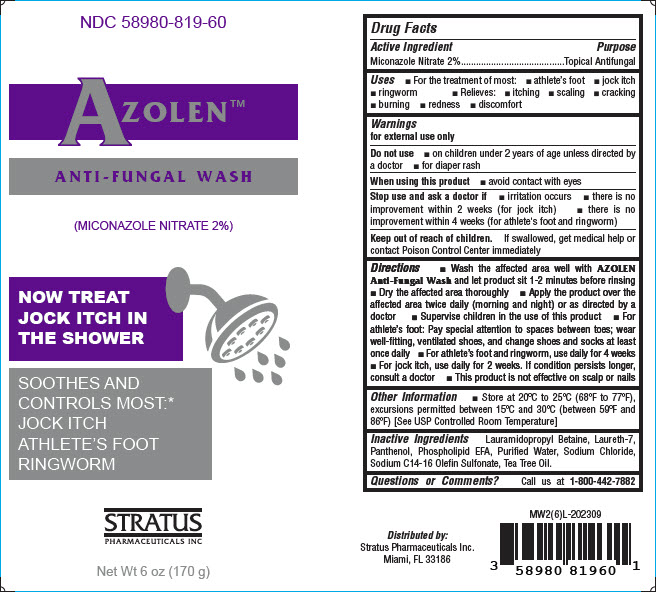 DRUG LABEL: AZOLEN
NDC: 58980-819 | Form: LIQUID
Manufacturer: STRATUS PHARMACEUTICALS INC
Category: otc | Type: HUMAN OTC DRUG LABEL
Date: 20241031

ACTIVE INGREDIENTS: MICONAZOLE NITRATE 2 mg/1 g
INACTIVE INGREDIENTS: SODIUM CHLORIDE; PANTHENOL; TEA TREE OIL; LAURETH-7; SODIUM C14-16 OLEFIN SULFONATE; LAURAMIDOPROPYL BETAINE; LINOLEAMIDOPROPYL PROPYLENE GLYCOL-DIMONIUM CHLORIDE PHOSPHATE; WATER

AZOLEN™

Drug Facts

Active Ingredient

Miconazole Nitrate 2%

Purpose

Topical Antifungal

Uses

- For the treatment of most:
  - athlete's foot
  - jock itch
  - ringworm
- Relieves:
  - itching
  - scaling
  - cracking
  - burning
  - redness
  - discomfort

Warnings

for external use only

Do not use

- on children under 2 years of age unless directed by a doctor
- for diaper rash

When using this product

- avoid contact with eyes

Stop use and ask a doctor if

- irritation occurs
- there is no improvement within 2 weeks (for jock itch)
- there is no improvement within 4 weeks (for athlete's foot and ringworm)

Keep out of reach of children. If swallowed, get medical help or contact Poison Control Center immediately

Directions

- Wash the affected area well with AZOLEN Anti-Fungal Wash and let product sit 1-2 minutes before rinsing
- Dry the affected area thoroughly
- Apply the product over the affected area twice daily (morning and night) or as directed by a doctor
- Supervise children in the use of this product
- For athlete's foot: Pay special attention to spaces between toes; wear well-fitting, ventilated shoes, and change shoes and socks at least once daily
- For athlete's foot and ringworm, use daily for 4 weeks
- For jock itch, use daily for 2 weeks. If condition persists longer, consult a doctor
- This product is not effective on scalp or nails

Other Information

- Store at 20°C to 25°C (68°F to 77°F), excursions permitted between 15°C and 30°C (between 59°F and 86°F) [See USP Controlled Room Temperature]

Inactive Ingredients

Lauramidopropyl Betaine, Laureth-7, Panthenol, Phospholipid EFA, Purified Water, Sodium Chloride, Sodium C14-16 Olefin Sulfonate, Tea Tree Oil.

Questions or Comments?

Call us at 1-800-442-7882

Distributed by:
Stratus Pharmaceuticals Inc.
Miami, FL 33186

PRINCIPAL DISPLAY PANEL - 170 g Bottle Box

NDC 58980-819-60

AZOLEN™
ANTI-FUNGAL WASH

(MICONAZOLE NITRATE 2%)

NOW TREAT
JOCK ITCH IN
THE SHOWER

SOOTHES AND
CONTROLS MOST:*
JOCK ITCH
ATHLETE'S FOOT
RINGWORM

STRATUS
PHARMACEUTICALS INC

Net Wt 6 oz (170 g)